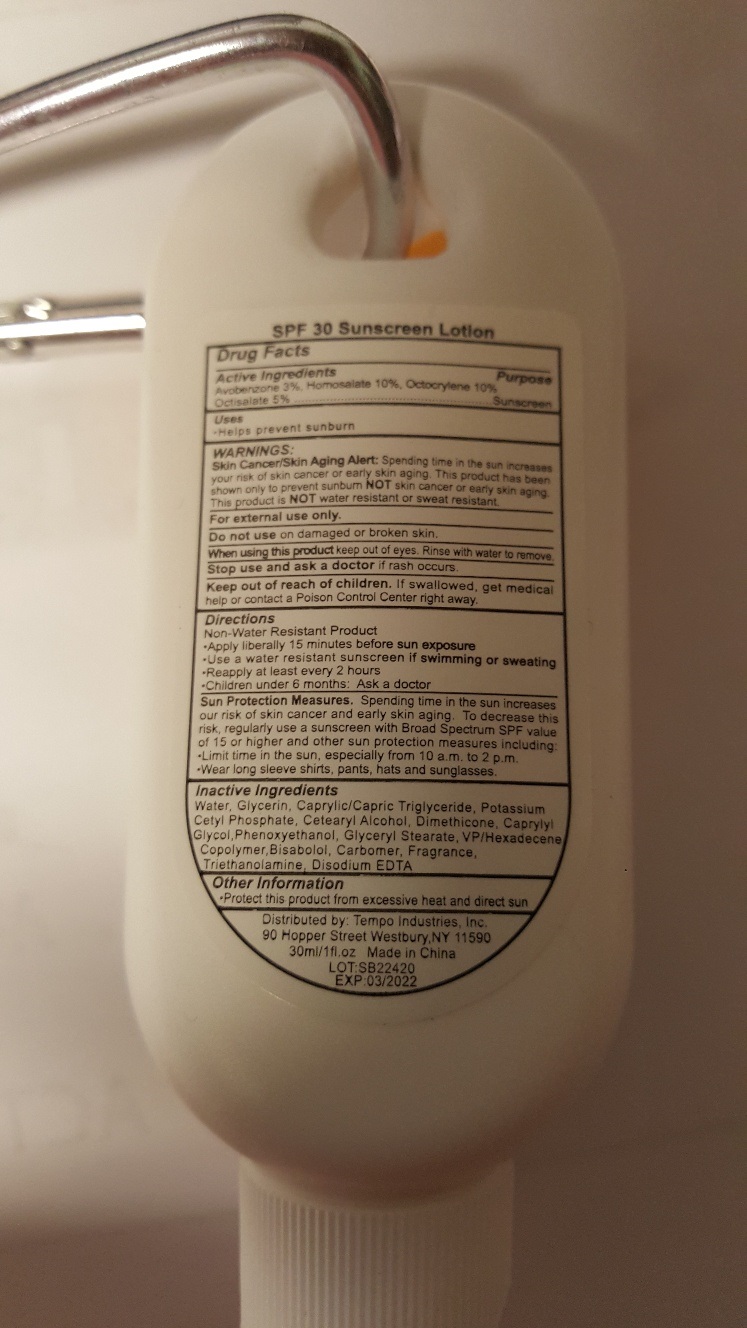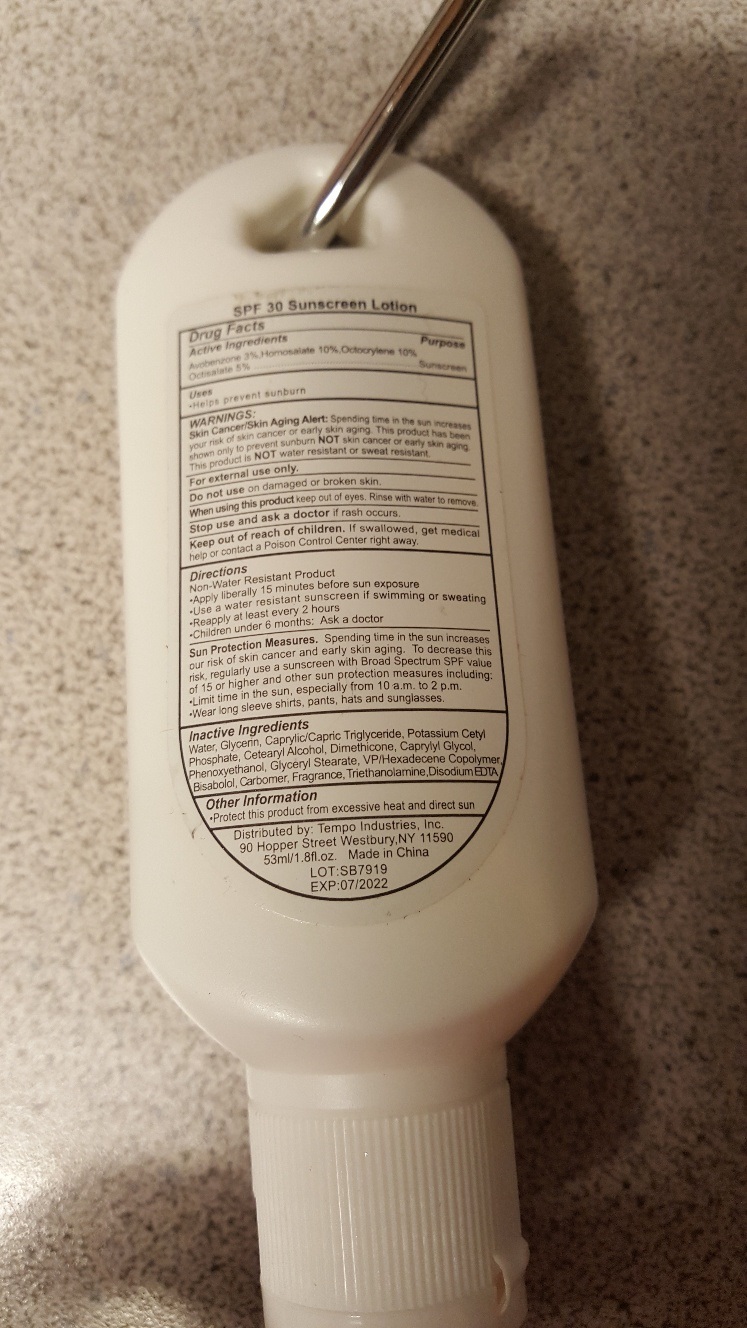 DRUG LABEL: Sunscreen SPF 30
NDC: 80524-002 | Form: LOTION
Manufacturer: Tempo Industries, Inc.
Category: otc | Type: HUMAN OTC DRUG LABEL
Date: 20250108

ACTIVE INGREDIENTS: AVOBENZONE 30 mg/1 mL; HOMOSALATE 100 mg/1 mL; OCTOCRYLENE 100 mg/1 mL; OCTISALATE 50 mg/1 mL
INACTIVE INGREDIENTS: WATER; GLYCERIN; MEDIUM-CHAIN TRIGLYCERIDES; POTASSIUM CETYL PHOSPHATE; CETOSTEARYL ALCOHOL; DIMETHICONE; CAPRYLYL GLYCOL; PHENOXYETHANOL; GLYCERYL MONOSTEARATE; VINYLPYRROLIDONE/HEXADECENE COPOLYMER; LEVOMENOL; CARBOMER HOMOPOLYMER, UNSPECIFIED TYPE; TROLAMINE; EDETATE DISODIUM ANHYDROUS

Sunscreen SPF 30

Active Ingredients

Avobenzone 3%, Homosalate 10%, Octocrylene 10%, Octisalate 5%

Purpose

Sunscreen

Uses

- Helps prevent sunburn

WARNINGS:

Spending time in the sun increases your risk of skin cancer or early skin aging. This product has been shown only to prevent sunburn skin cancer or early skin aging. This product is water resistant or sweat resistant. Skin Cancer/Skin Aging Alert: NOTNOT

For external use only.

Do not use

on damaged or broken skin.

When using this product

keep out of eyes. Rinse with water to remove.

Stop use and ask a doctor

if rash occurs.

Keep out of reach of children.

If swallowed, get medical help or contact a Poison Control Center right away.

Directions

Non-Water Resistant Product

Spending time in the sun increases our risk of skin cancer and early skin aging. To decrease this risk, regularly use a sunscreen with Broad Spectrum SPF value of 15 or higher and other sun protection measuress including: Sun Protection Measures.

- Apply liberally 15 minutes before sun exposure
- Use a water resistant sunscreen if swimming or sweating
- Reapply at least every 2 hours
- Children under 6 months: Ask a doctor

- Limit time in the sun, especially from 10 a.m. to 2 p.m.
- Wear long sleeve shirts, pants, hats and sunglasses.

Inactive Ingredients

Water, Glycerin, Caprylic/Capric Triglyceride, Potassium Cetyl Phosphate, Cetearyl Alcohol, Dimethicone, Caprylyl Glycol, Phenoxyethanol, Glyceryl Stearate, VP/Hexadecene Copolymer, Bisabolol, Carbomer, Fragrance, Triethanolamine, Disodium EDTA

Other Information

- Protect this product from excessive heat and direct sun